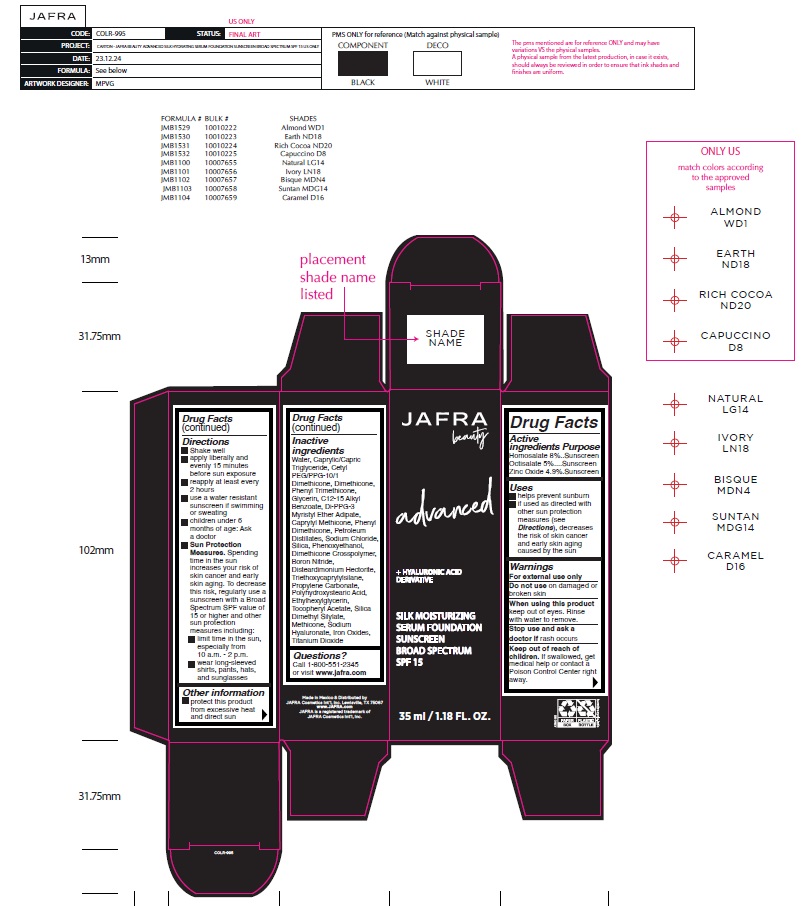 DRUG LABEL: JAFRA Beauty advanced SILK MOISTURIZING SERUM FOUNDATION SUNSCREEN BROAD SPECTRUM SPF 15 CARAMEL D16
NDC: 68828-313 | Form: LIQUID
Manufacturer: Distribuidora Comercial Jafra, S.A. de C.V.
Category: otc | Type: HUMAN OTC DRUG LABEL
Date: 20250203

ACTIVE INGREDIENTS: HOMOSALATE 8 g/100 mL; OCTISALATE 5 g/100 mL; ZINC OXIDE 4.9 g/100 mL
INACTIVE INGREDIENTS: ETHYLHEXYLGLYCERIN; CETYL PEG/PPG-10/1 DIMETHICONE (HLB 5); GLYCERIN; POLYHYDROXYSTEARIC ACID STEARATE; DIMETHICONE; PHENYL TRIMETHICONE; PHENOXYETHANOL; BORON NITRIDE; FERRIC OXIDE YELLOW; TITANIUM DIOXIDE; TRIETHOXYCAPRYLYLSILANE; SILICA; PROPYLENE CARBONATE; MEDIUM-CHAIN TRIGLYCERIDES; ALKYL (C12-15) BENZOATE; CAPRYLYL METHICONE; DIMETHICONE CROSSPOLYMER; METHICONE (20 CST); SODIUM HYALURONATE; WATER; DI-PPG-3 MYRISTYL ETHER ADIPATE; DISTEARDIMONIUM HECTORITE; .ALPHA.-TOCOPHEROL ACETATE; FERRIC OXIDE RED; FERROSOFERRIC OXIDE; SODIUM CHLORIDE; SILICA DIMETHYL SILYLATE

Active Ingredients

Homosalate 8%

Octisalate 5%

Zinc Oxide 4.9%

Purpose

Sunscreen

Uses

- helps prevent sunburn
- if used as directed with other sun protection measures (see Directions), decreases the risk of skin cancer and early skin aging caused by the sun

Warnings

For external use only

Do not useon damaged or broken skin

When using this productkeep out of eyes. Rinse with water to remove.

Stop use and ask a doctorifrash occurs

Keep out of reach of children.If swallowed, get medical help or contact a Poison Control Center right away.

Directions

- Shake well
- apply liberally and evenly 15 minutes before sun exposure
- reapply at least every 2 hours
- use a water resistant sunscreen if swimming or sweating
- children under 6 months of age: Ask a doctor
- Sun Protection Measures.Spending time in the sun increases your risk of skin cancer and early skin aging. To decrease this risk, regularly use a sunscreen with a Broad Spectrum SPF value of 15 or higher and other sun protection measures including:

• limit time in the sun, especially from 10 a.m. – 2 p.m.

• wear long-sleeved shirts, pants, hats, and sunglasses

Other information

- protect this product from excessive heat and direct sun

Inactive Ingredients

Water, Caprylic/Capric Triglyceride, Cetyl PEG/PPG-10/1 Dimethicone, Dimethicone, Phenyl Trimethicone, Glycerin, C12-15 Alkyl Benzoate, Di-PPG-3 Myristyl Ether Adipate, Caprylyl Methicone, Phenyl Dimethicone, Petroleum Distillates, Sodium Chloride, Silica, Phenoxyethanol, Dimethicone Crosspolymer, Boron Nitride, Disteardimonium Hectorite, Triethoxycaprylylsilane, Propylene Carbonate, Polyhydroxystearic Acid, Ethylhexylglycerin, Tocopheryl Acetate, Silica Dimethyl Silylate, Methicone, Sodium Hyaluronate, Iron Oxides, Titanium Dioxide

Questions ?

Call 1-800-551-2345 or visit www.jafra.com